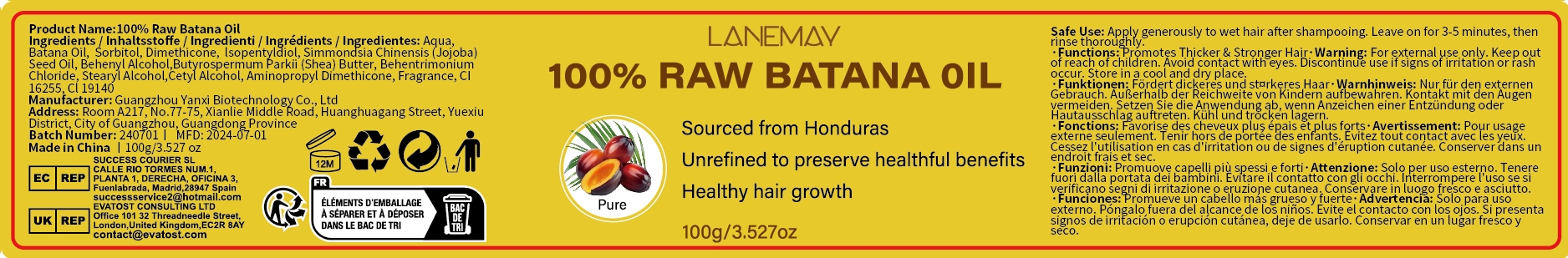 DRUG LABEL: 100% Raw Batana Oil
NDC: 84025-237 | Form: CREAM
Manufacturer: Guangzhou Yanxi Biotechnology Co., Ltd
Category: otc | Type: HUMAN OTC DRUG LABEL
Date: 20241028

ACTIVE INGREDIENTS: SORBITOL 5 mg/100 g; DIMETHICONE 3 mg/100 g
INACTIVE INGREDIENTS: WATER

DOSAGE AND ADMINISTRATION

Apply generously to wet hair after shampooing.Leave on for 3-5 minutes,then rinse thoroughly.

WARNINGS

Keep out of children

INACTIVE INGREDIENT

Aqua

INDICATIONS AND USAGE

For daily hair care

Keep out of children

PURPOSE

Healthy hair growth